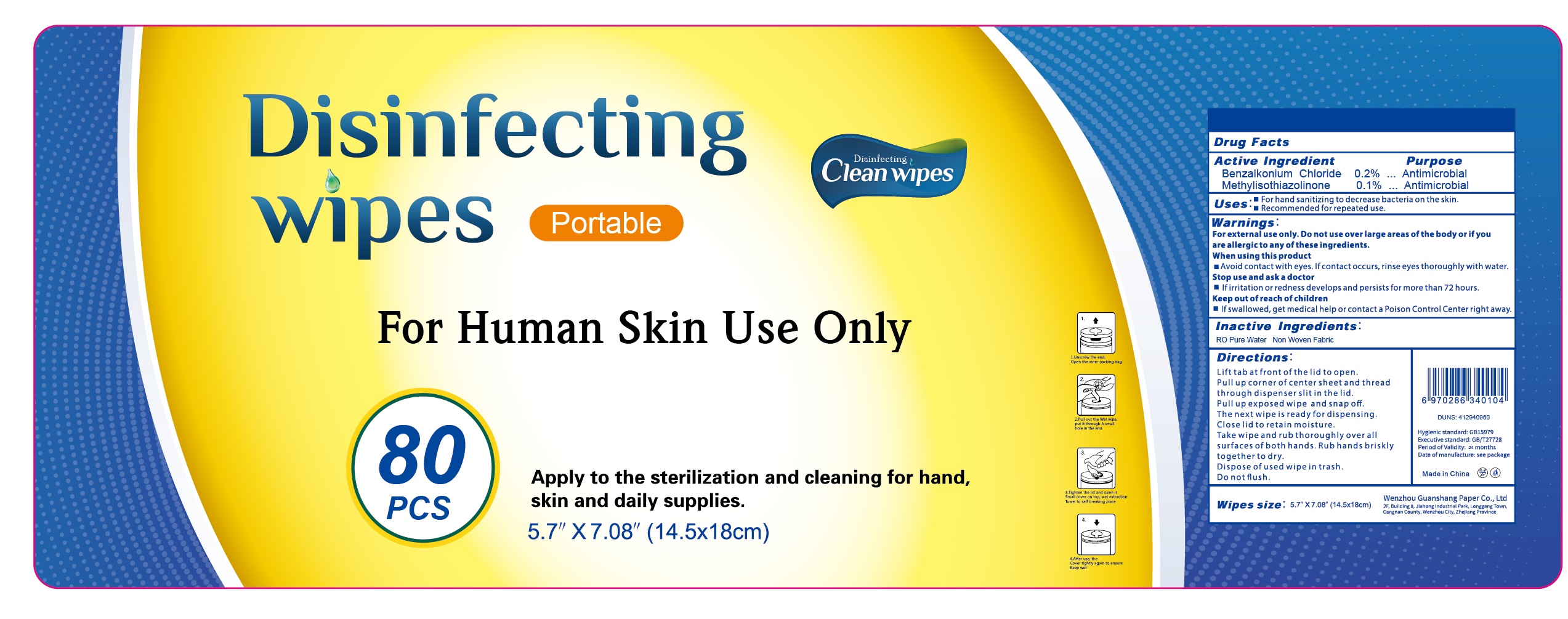 DRUG LABEL: Disinfecting Wipes
NDC: 78122-080 | Form: CLOTH
Manufacturer: Wenzhou Guanshang Paper Co., Ltd
Category: otc | Type: HUMAN OTC DRUG LABEL
Date: 20200803

ACTIVE INGREDIENTS: BENZALKONIUM CHLORIDE 0.2 g/100 1; METHYLISOTHIAZOLINONE 0.1 g/100 1
INACTIVE INGREDIENTS: WATER

78122-080 Guanshang,Disinfecting Wipes,

Active ingredient

BENZALKONIUM CHLORIDE,METHYLISOTHIAZOLINONE.

Purpose

Antimicrobial.

Indications & usage

- For hand sanitizing to decrease bacteria on the skin.
- Recommended for repeated use.

Warnings

For external use only.Do not use over large areas of the body or if you are allergic to any of these ingredients.

When using

Avoid contact with eyes.If contact occurs,rinse eyes thoroughly with water.

Stop use

Stop use and ask a doctor if irritation or redness develops and persists for more than 72 hours.

Keep out of reach of children

If swallowed, get medical help or contact a Poison Control Center right away.

Inactive ingredient

RO Pure Water,Non Woven Fabric.

Do not use

if you are allergic to any of the ingredients.

Directions

Lift tab ag front of the lid to open.

Pull up corner of center sheet an thread through dispenser slit in the lid.

Pull up expossed wipe and snap off.

The next wipe is ready for dispensing.

Close lid to retain moisture.

Take wipe and rub thoroughly over all surfaces of both hands.Rub hands briskly together to dry.

Dispose of used wipe in trash.

Do not flush.